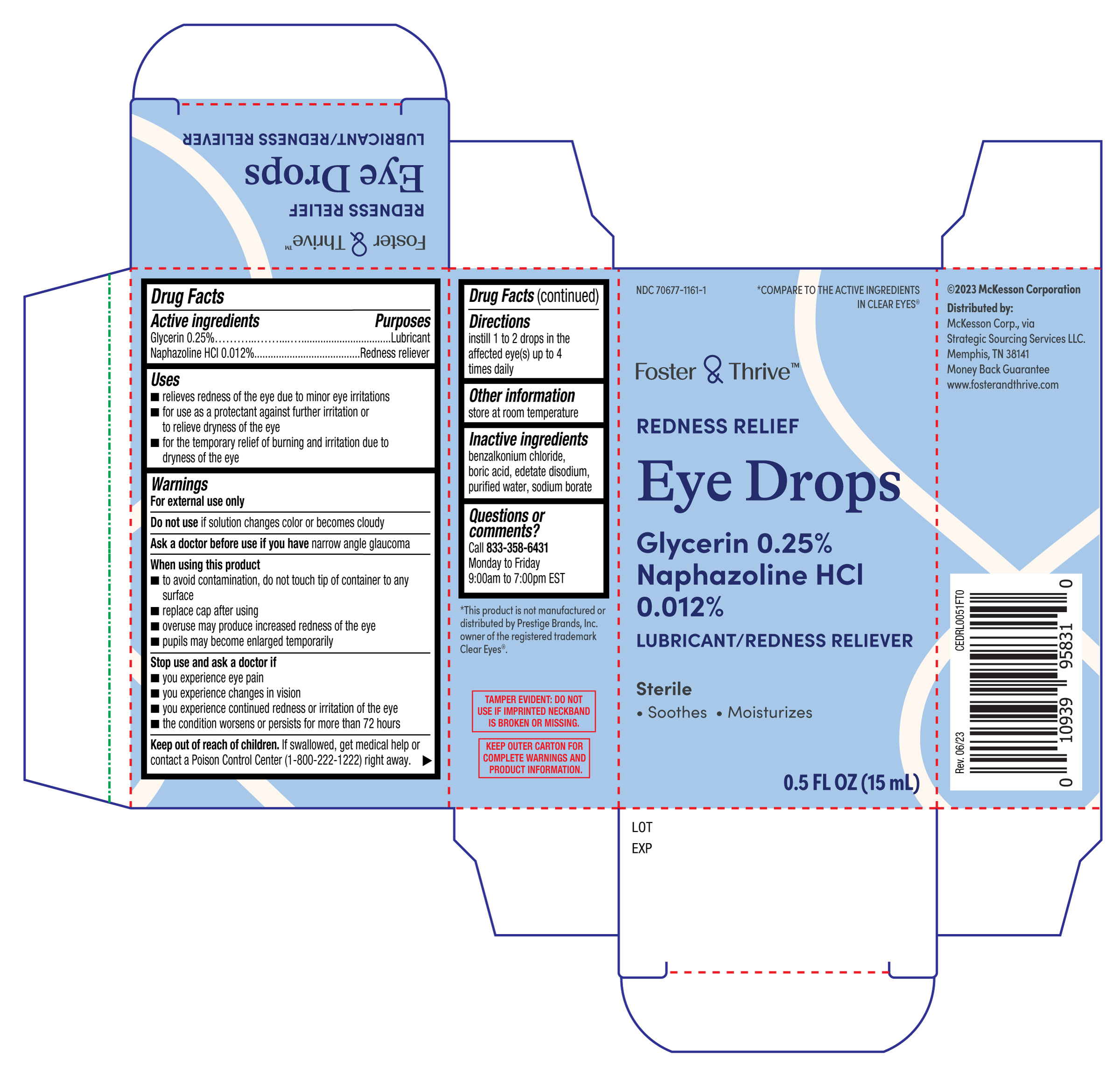 DRUG LABEL: Foster and Thrive Redness Relief Eye Drops
NDC: 70677-1161 | Form: SOLUTION/ DROPS
Manufacturer: Strategic Sourcing Services LLC
Category: otc | Type: HUMAN OTC DRUG LABEL
Date: 20251230

ACTIVE INGREDIENTS: NAPHAZOLINE HYDROCHLORIDE 0.012 g/100 mL; GLYCERIN 0.25 g/100 mL
INACTIVE INGREDIENTS: WATER; SODIUM BORATE; BENZALKONIUM CHLORIDE; EDETATE DISODIUM; BORIC ACID

Foster and Thrive Redness Relief Eye Drops 15mL (PLD)

Active ingredients

Glycerin 0.25%

Naphazoline HCl 0.012%

Purposes

Lubricant

Redness reliever

Uses

- relieves redness of the eye due to minor eye irritations
- for use as a protectant against further irritation or to relieve dryness of the eye
- for the temporary relief of burning and irritation due to dryness of the eye

Warnings

For external use only

Do not use

if solution changes color or becomes cloudy

Ask a doctor before use if you have

narrow angle glaucoma

When using this product

- to avoid contamination, do not touch tip of container to any surface
- replace cap after using
- overuse may produce increased redness of the eye
- pupils may become enlarged temporarily

Stop use and ask a doctor if

- you experience eye pain
- you experience changes in vision
- you experience continued redness or irritation of the eye
- the condition worsens or persists for more than 72 hours

Keep out of reach of children.

If swallowed, get medical help or contact a Poison Control Center (1-800-222-1222) right away.

Directions

instill 1 to 2 drops in the affected eye(s) up to 4 times daily

Other information

store at room temperature

Inactive ingredients

benzalkonium chloride, boric acid, edetate disodium, purified water, sodium borate

Questions or comments?

Call 833-358-6431

Monday to Friday

9:00am to 7:00pm EST